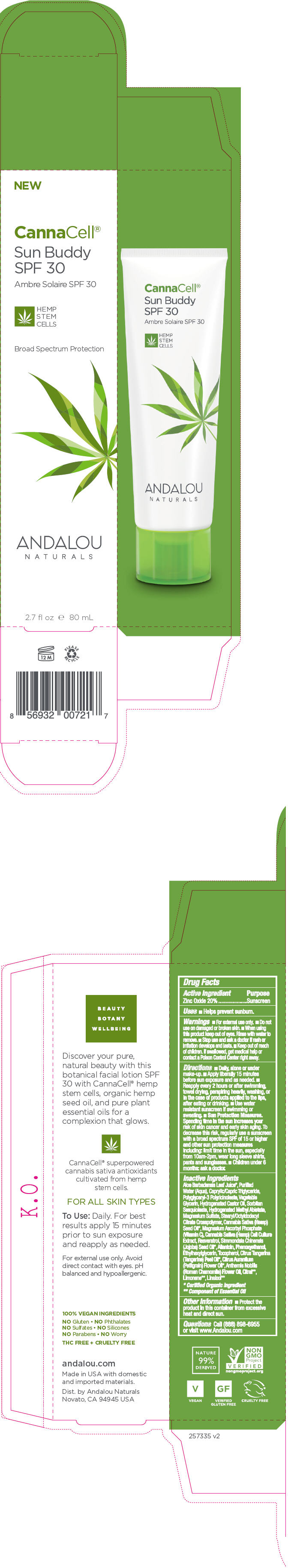 DRUG LABEL: CannaCell Sun Buddy Facial SPF 30
NDC: 55560-1812 | Form: LOTION
Manufacturer: Andalou naturals
Category: otc | Type: HUMAN OTC DRUG LABEL
Date: 20200117

ACTIVE INGREDIENTS: ZINC OXIDE 200 mg/1 mL
INACTIVE INGREDIENTS: ALOE VERA LEAF; WATER; MEDIUM-CHAIN TRIGLYCERIDES; POLYGLYCERYL-3 RICINOLEATE; GLYCERIN; HYDROGENATED CASTOR OIL; SORBITAN SESQUIOLEATE; HYDROGENATED METHYL ABIETATE; MAGNESIUM SULFATE, UNSPECIFIED FORM; OCTYLDODECYL STEARATE; CANNABIS SATIVA SEED OIL; MAGNESIUM ASCORBYL PHOSPHATE; CANNABIS SATIVA WHOLE; RESVERATROL; JOJOBA OIL; ALLANTOIN; PHENOXYETHANOL; ETHYLHEXYLGLYCERIN; TOCOPHEROL; MANDARIN OIL; CITRUS AURANTIUM FLOWER OIL; CHAMAEMELUM NOBILE FLOWER OIL

CannaCell® Sun Buddy Facial SPF 30

Drug Facts

Active Ingredient

Zinc Oxide 20%

Purpose

Sunscreen

Uses

- Helps prevent sunburn.

Warnings

- For external use only.

- Do not use on damaged or broken skin.

- When using this product keep out of eyes. Rinse with water to remove.

- Stop use and ask a doctor if rash or irritation develops and lasts.

- Keep out of reach of children. If swallowed, get medical help or contact a Poison Control Center right away.

Directions

- Daily, alone or under make-up.
- Apply liberally 15 minutes before sun exposure and as needed.
- Reapply every 2 hours or after swimming, towel drying, perspiring heavily, washing, or in the case of products applied to the lips, after eating or drinking.
- Use water resistant sunscreen if swimming or sweating.
- Sun Protection Measures. Spending time in the sun increases your risk of skin cancer and early skin aging. To decrease this risk, regularly use a sunscreen with a broad spectrum SPF of 15 or higher and other sun protection measures including: limit time in the sun, especially from 10am-2pm, wear long sleeve shirts, pants and sunglasses.
- Children under 6 months: ask a doctor.

Inactive Ingredients

Aloe Barbadensis Leaf Juice [Certified Organic Ingredient] , Purified Water (Aqua), Caprylic/Capric Triglyceride, Polyglyceryl-3 Polyricinoleate, Vegetable Glycerin, Hydrogenated Castor Oil, Sorbitan Sesquioleate, Hydrogenated Methyl Abietate, Magnesium Sulfate, Stearyl/Octyldodecyl Citrate Crosspolymer, Cannabis Sativa (Hemp) Seed Oil, Magnesium Ascorbyl Phosphate (Vitamin C), Cannabis Sativa (Hemp) Cell Culture Extract, Resveratrol, Simmondsia Chinensis (Jojoba) Seed Oil, Allantoin, Phenoxyethanol, Ethylhexylglycerin, Tocopherol, Citrus Tangerina (Tangerine) Peel Oil, Citrus Aurantium (Petitgrain) Flower Oil, Anthemis Nobilis (Roman Chamomile) Flower Oil, Citral [Component of Essential Oil] , Limonene, Linalool

Other Information

- Protect the product in this container from excessive heat and direct sun.

Questions

Call (888) 898-6955 or visit www.Andalou.com

Dist. by Andalou Naturals
Novato, CA 94945 USA

PRINCIPAL DISPLAY PANEL - 80 mL Tube Carton

NEW

CannaCell®

Sun Buddy
SPF 30

HEMP
STEM
CELLS

Broad Spectrum Protection

ANDALOU
NATURALS

2.7 fl oz e 80 mL